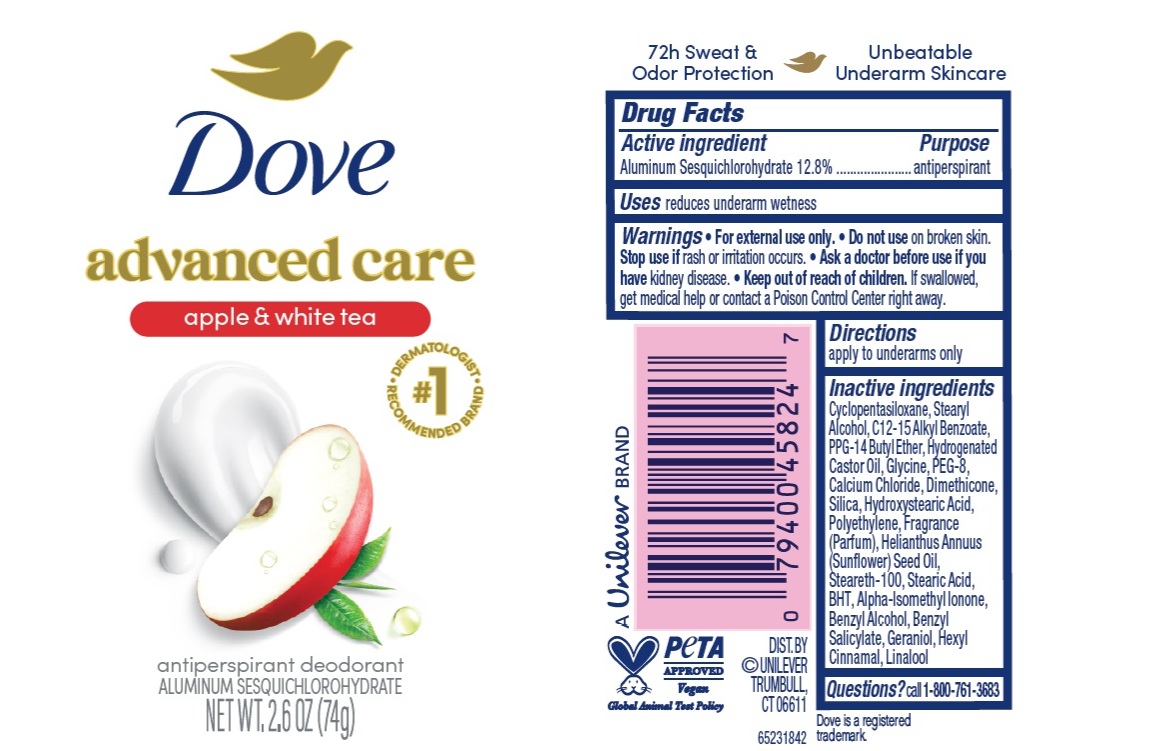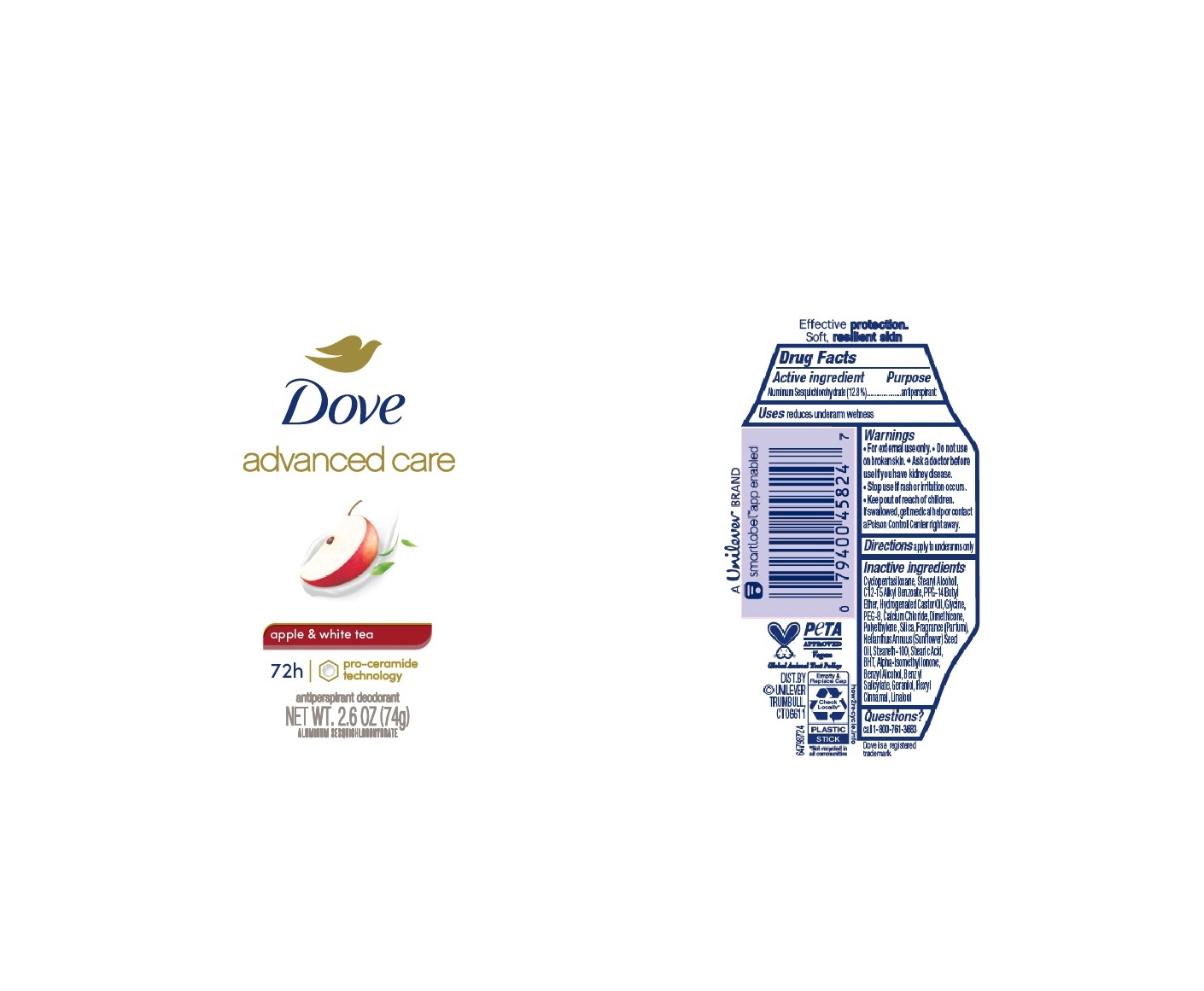 DRUG LABEL: Dove
NDC: 64942-2336 | Form: STICK
Manufacturer: Conopco Inc. d/b/a/ Unilever
Category: otc | Type: HUMAN OTC DRUG LABEL
Date: 20260220

ACTIVE INGREDIENTS: ALUMINUM SESQUICHLOROHYDRATE 12.8 g/100 g
INACTIVE INGREDIENTS: ISOMETHYL-.ALPHA.-IONONE; BENZYL ALCOHOL; .ALPHA.-HEXYLCINNAMALDEHYDE; STEARIC ACID; CALCIUM CHLORIDE; HIGH DENSITY POLYETHYLENE; CYCLOMETHICONE 5; HYDROGENATED CASTOR OIL; BUTYLATED HYDROXYTOLUENE; PPG-14 BUTYL ETHER; STEARYL ALCOHOL; SUNFLOWER OIL; SILICON DIOXIDE; ALKYL (C12-15) BENZOATE; DIMETHICONE; STEARETH-100; POLYETHYLENE GLYCOL 400; LINALOOL, (+/-)-; GLYCINE; GERANIOL; BENZYL SALICYLATE

Dove Advanced Care Apple & White Tea 72h Antiperspirant Deodorant

Drug Facts

Active ingredient

Aluminum Sesquichlorohydrate (12.8)

Purpose

antiperspirant

Uses

reduces underarm wetness

Warnings

• For external use only.
• Do not use on broken skin .
• Ask a doctor before use if you have kidney disease.
• Stop use if rash or irritation occurs.

• Keep out of reach of children.

If swallowed, get medical help or contact a Poison Control Center right away.

Directions

apply to underarms only

Inactive ingredients

Cyclopentasiloxane, Stearyl Alcohol, C12-15 Alkyl Benzoate, PPG-14 Butyl Ether, Hydrogenated Castor Oil, Glycine, PEG-8, Calcium Chloride, Dimethicone, Polyethylene, Silica, Fragrance (Parfum), Helianthus Annuus (Sunflower) Seed Oil, Steareth-100, Stearic Acid, BHT, Alpha-Isomethyl Ionone, Benzyl Alcohol, Benzyl Salicylate, Geraniol, Hexyl Cinnamal, Linalool

Questions?

Call 1-800-761-3683